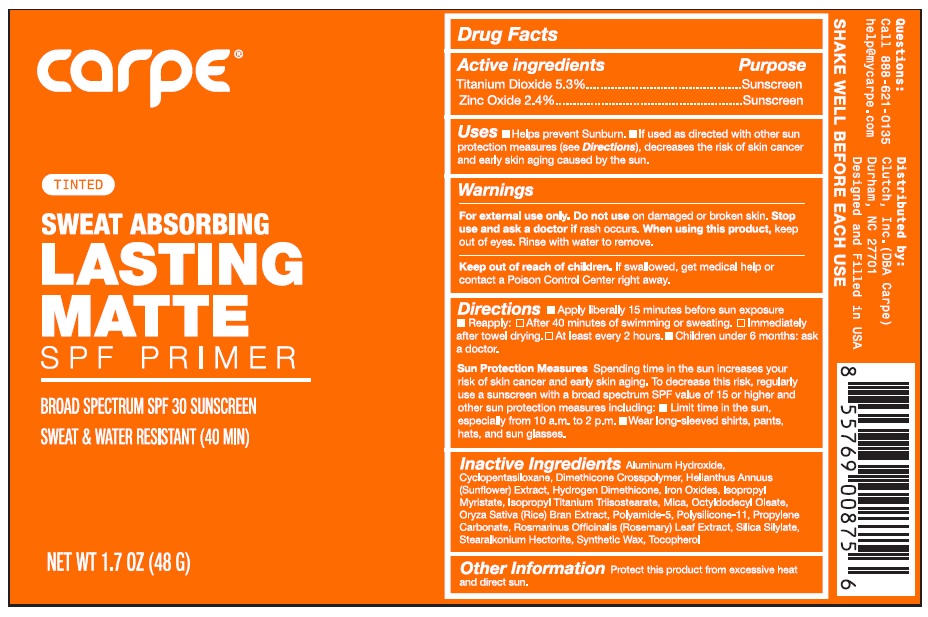 DRUG LABEL: Carpe SPF 30 Face Primer
NDC: 83306-414 | Form: LOTION
Manufacturer: Clutch, Inc. DBA Carpe
Category: otc | Type: HUMAN OTC DRUG LABEL
Date: 20241220

ACTIVE INGREDIENTS: TITANIUM DIOXIDE 5.3 g/100 g; ZINC OXIDE 2.4 g/100 g
INACTIVE INGREDIENTS: DIMETHICONE/VINYL DIMETHICONE CROSSPOLYMER (SOFT PARTICLE); PROPYLENE CARBONATE; TOCOPHEROL; SYNTHETIC WAX (1900 MW); HYDROGEN DIMETHICONE (30 CST); CYCLOMETHICONE 5; FERRIC OXIDE RED; FERRIC OXYHYDROXIDE; RICE BRAN; ISOPROPYL TITANIUM TRIISOSTEARATE; ISOPROPYL MYRISTATE; OCTYLDODECYL OLEATE; DIMETHICONE CROSSPOLYMER (450000 MPA.S AT 12% IN CYCLOPENTASILOXANE); HELIANTHUS ANNUUS FLOWERING TOP; STEARALKONIUM HECTORITE; POLYAMIDE-5; ROSEMARY; SILICA DIMETHYL SILYLATE; FERROSOFERRIC OXIDE; MICA

Carpe - Sweat Absorbing Lasting Matte SPF Primer (11-ER-077)

Active Ingredients

Titanium Dioxide – 5.3%
Zinc Oxide – 2.4%

Purpose

Sunscreen

Uses

• Helps prevent sunburn
• If used as directed with other sun protection measures (see Directions), decreases the risk of skin cancer and early skin aging caused by the sun.

Warnings

• For external use only.
• Do not useon damaged or broken skin.
• When using this productkeep out of eyes. Rinse with water to remove.
• Stop use and ask a doctor if rash occurs.

- Keep out of reach of children.If swallowed, get medical help or contact a Poison Control Center right away.

Directions

• Apply liberally 15 minutes before sun exposure.

• Reapply: • After 40 minutes of swimming or sweating. • Immediately after towel drying. • At least every 2 hours.

• Children under six months: Ask a doctor.
• Sun Protection Measures:Spending time in the sun increases your risk of skin cancer and early skin aging. To decrease this risk, regularly use a sunscreen with a Broad Spectrum SPF value of 15 or higher and other sun protection measures including: • Limit time in the sun especially from 10 a.m. – 2 p.m. • Wear long-sleeved shirts, pants, hats, and sunglasses.

Inactive Ingredients

Aluminum Hydroxide, Cyclopentasiloxane, Dimethicone Crosspolymer, Helianthus Annuus (Sunflower) Extract, Hydrogen Dimethicone, Iron Oxides, Isopropyl Myristate, Isopropyl Titanium Triisostearate, Mica, Octyldodecyl Oleate, Oryza Sativa (Rice) Bran Extract, Polyamide-5, Polysilicone-11, Propylene Carbonate, Rosmarinus Officinalis (Rosemary) Leaf Extract, Silica Silylate, Stearalkonium Hectorite, Synthetic Wax, Tocopherol

Other Information

Protect this product fro excessive heat and direct sun.